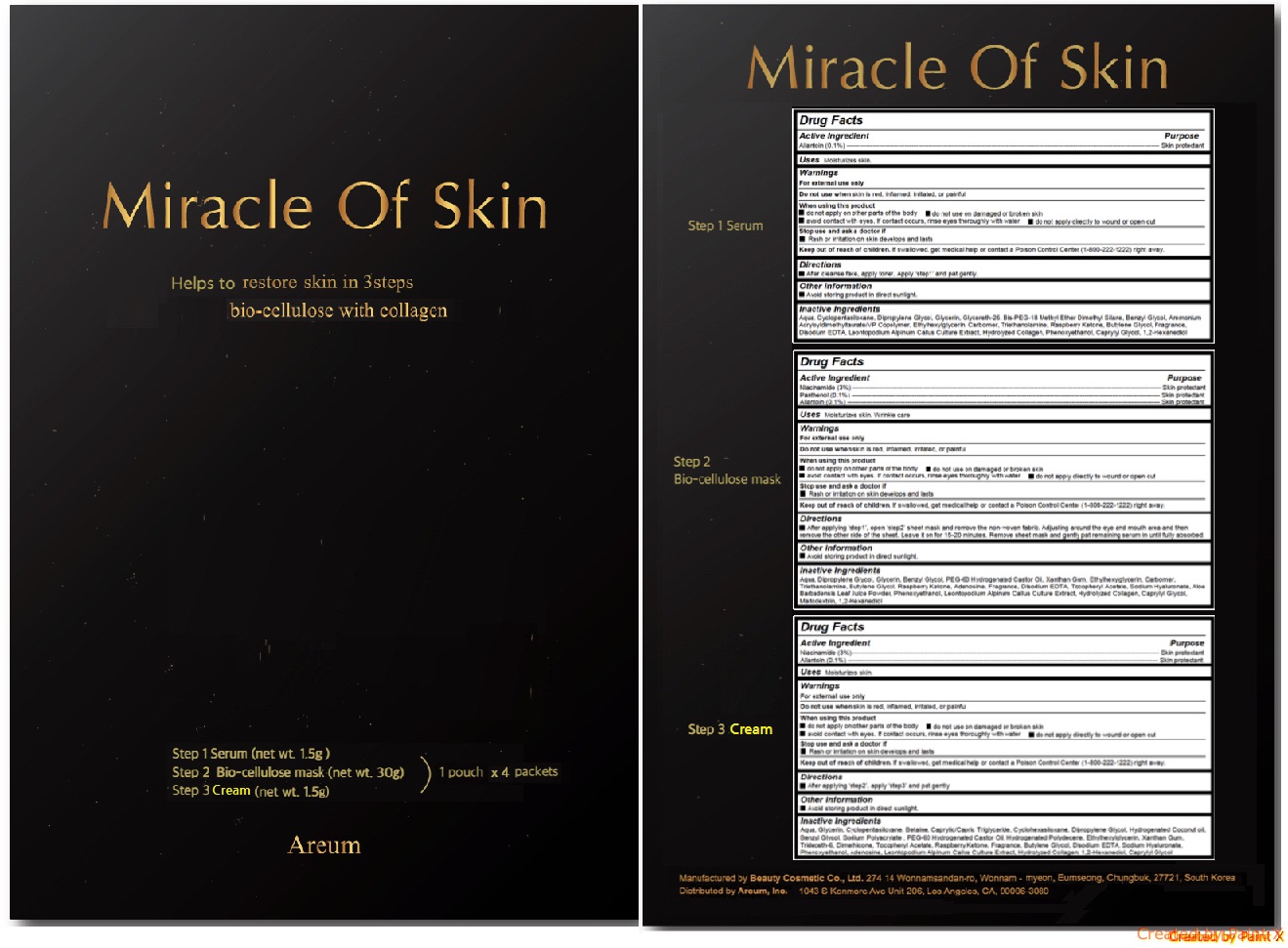 DRUG LABEL: Miracle Of Skin
NDC: 72148-103 | Form: KIT | Route: TOPICAL
Manufacturer: Areum, Inc.
Category: otc | Type: HUMAN OTC DRUG LABEL
Date: 20180323

ACTIVE INGREDIENTS: allantoin 0.0015 g/1.5 g; NIACINAMIDE 0.9 g/30 g; PANTHENOL 0.03 g/30 g; Allantoin 0.03 g/30 g; NIACINAMIDE 0.045 g/1.5 g; allantoin 0.0015 g/1.5 g
INACTIVE INGREDIENTS: water; Dipropylene Glycol; Glycerin; BIS-PEG-18 METHYL ETHER DIMETHYL SILANE	; ETHYLENE GLYCOL MONOBENZYL ETHER; AMMONIUM ACRYLOYLDIMETHYLTAURATE/VP COPOLYMER; ETHYLHEXYLGLYCERIN; CARBOXYPOLYMETHYLENE; TROLAMINE; 4-(P-HYDROXYPHENYL)-2-BUTANONE; BUTYLENE GLYCOL; EDETATE DISODIUM ANHYDROUS; PHENOXYETHANOL; CAPRYLYL GLYCOL; 1,2-Hexanediol; water; Dipropylene Glycol; Glycerin; ETHYLENE GLYCOL MONOBENZYL ETHER; PEG-60 Hydrogenated Castor Oil; Xanthan Gum; Ethylhexylglycerin; CARBOXYPOLYMETHYLENE; TROLAMINE; Butylene Glycol; EDETATE DISODIUM ANHYDROUS; .ALPHA.-TOCOPHEROL ACETATE; HYALURONATE SODIUM; ALOE VERA LEAF; Phenoxyethanol; CAPRYLYL GLYCOL	; Maltodextrin; 1,2-Hexanediol; 4-(P-HYDROXYPHENYL)-2-BUTANONE; water; Glycerin; CYCLOMETHICONE 5; Betaine; MEDIUM-CHAIN TRIGLYCERIDES; CYCLOMETHICONE 6; Dipropylene Glycol; Hydrogenated Coconut oil; ETHYLENE GLYCOL MONOBENZYL ETHER; SODIUM POLYACRYLATE (2500000 MW); PEG-60 Hydrogenated Castor Oil; HYDROGENATED POLYDECENE (550 MW); Ethylhexylglycerin; Xanthan Gum; Trideceth-6; Dimethicone; .ALPHA.-TOCOPHEROL ACETATE; 4-(P-HYDROXYPHENYL)-2-BUTANONE; Butylene Glycol; EDETATE DISODIUM ANHYDROUS; HYALURONATE SODIUM; Phenoxyethanol; Adenosine; 1,2-HEXANEDIOL; Caprylyl Glycol

Miracle Of Skin

Active ingredients

Step 1 Serum - Allantoin (0.1%)

Step 2 Bio-cellulose mask - Niacinamide (3%), Panthenol (0.1%), Allantoin (0.1%)

Step 3 Cream - Niacinamide (3%), Allantoin (0.1%)

Purpose

Skin portectant

Keep out of reach of children

If swallowed, get medical help or contact a Poison Control Center (1-800-222-1222) right away.

Uses

Step 1 Serum - Moisturize skin.

Step 2 Bio-cellulose mask - Moisturize skin. Wrinkle care.

Step 3 Serum - Moisturize skin.

Warnings

For external use only

Do not use when skin is red, inflamed, irritated, or painful

When using this product

- do not apply on other parts of the body
- do not use on damaged or broken skin
- avoid contact with eyes. If contact occurs, rinse eyes thoroughly with water
- do not apply directly to wound or open cut

Stop use and ask a doctor if

- Rash or irritation on skin develops and lasts

Directions

Step 1 Serum - After cleanse face, apply toner. Apply ‘step1’ and pat gently.

Step 2 Bio-cellulose mask - After applying ‘step1’, open ‘step2’ sheet mask and remove the non-woven fabric. Adjusting around the eye and mouth area and then remove the other side of the sheet. Leave it on for 15-20 minutes. Remove sheet mask and gently pat remaining serum in until fully absorbed.

Step 3 Serum - After applying ‘step2’, apply ‘step3’ and pat gently.

INACTIVE INGREDIENT

Step 1 Serum - Aqua, Cyclopentasiloxane, Dipropylene Glycol, Glycerin, Glycereth-26, Bis-PEG-18 Methyl Ether Dimethyl Silane, Benzyl Glycol, Ammonium Acryloyldimethyltaurate/VP Copolymer, Ethylhexylglycerin, Carbomer, Triethanolamine, Raspberry Ketone, Butylene Glycol, Fragrance, Disodium EDTA, Leontopodium Alpinum Callus Culture Extract, Hydrolyzed Collagen, Phenoxyethanol, Caprylyl Glycol, 1,2-Hexanediol

Step 2 Bio-cellulose mask - Aqua, Dipropylene Glycol, Glycerin, Benzyl Glycol, PEG-60 Hydrogenated Castor Oil, Xanthan Gum, Ethylhexylglycerin, Carbomer, Triethanolamine, Butylene Glycol, Raspberry Ketone, Adenosine, Fragrance, Disodium EDTA, Tocopheryl Acetate, Sodium Hyaluronate, Aloe Barbadensis Leaf Juice Powder, Phenoxyethanol, Leontopodium Alpinum Callus Culture Extract, Hydrolyzed Collagen, Caprylyl Glycol, Maltodextrin, 1,2-Hexanediol

Step 3 Serum - Aqua, Glycerin, Cyclopentasiloxane, Betaine, Caprylic/Capric Triglyceride, Cyclohexasiloxane, Dipropylene Glycol, Hydrogenated Coconut oil, Benzyl Glycol, Sodium Polyacrylate , PEG-60 Hydrogenated Castor Oil, Hydrogenated Polydecene, Ethylhexylglycerin, Xanthan Gum, Trideceth-6, Dimethicone, Tocopheryl Acetate, Raspberry Ketone, Fragrance, Butylene Glycol, Disodium EDTA, Sodium Hyaluronate, Phenoxyethanol, Adenosine, Leontopodium Alpinum Callus Culture Extract, Hydrolyzed Collagen, 1,2-Hexanediol, Caprylyl Glycol